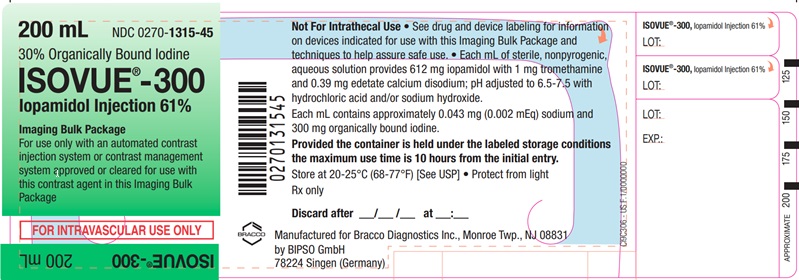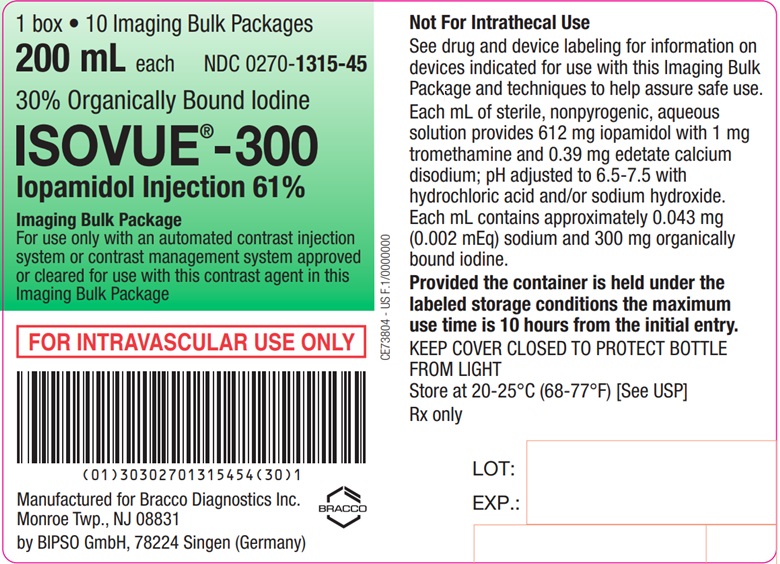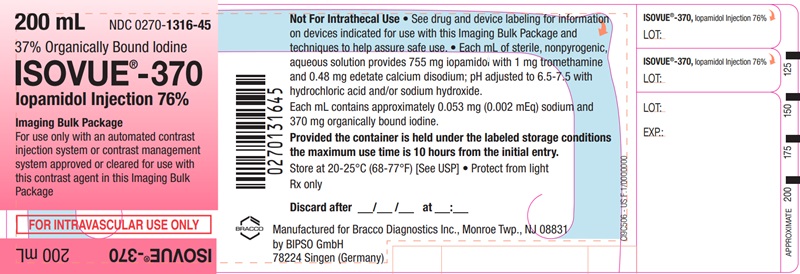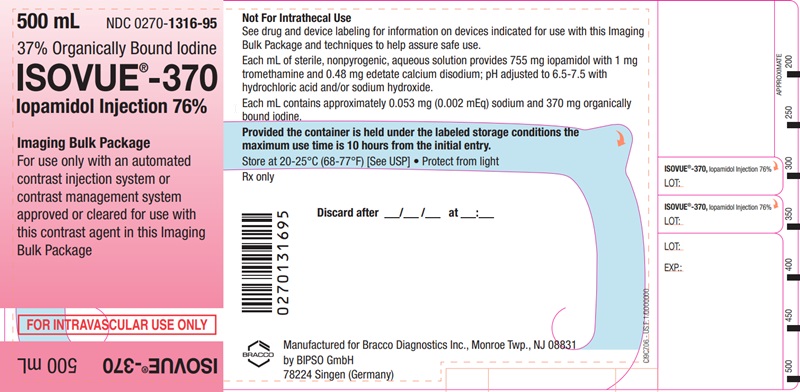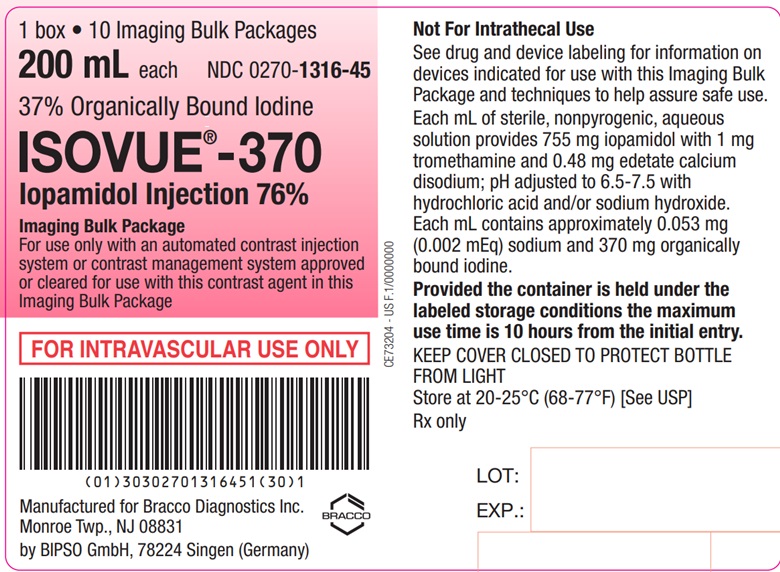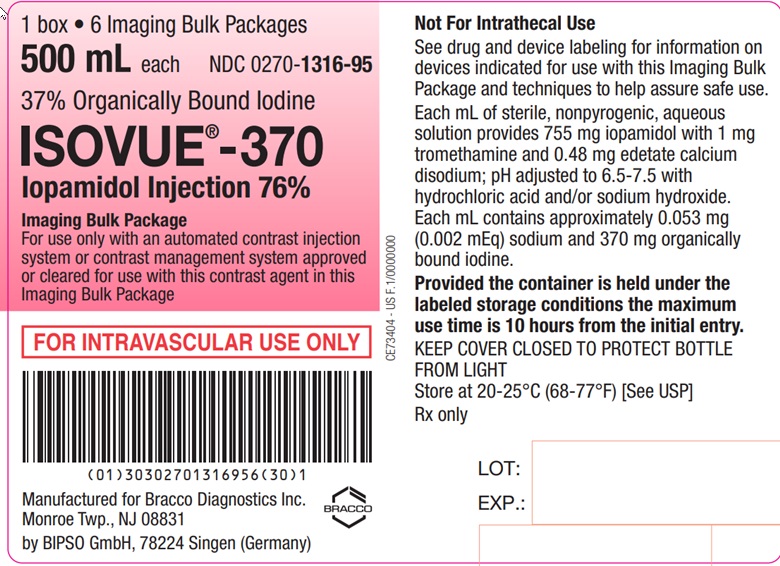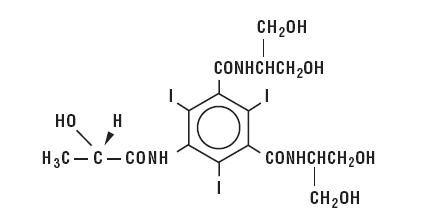 DRUG LABEL: ISOVUE
NDC: 0270-1315 | Form: INJECTION, SOLUTION
Manufacturer: Bracco Diagnostics Inc
Category: prescription | Type: HUMAN PRESCRIPTION DRUG LABEL
Date: 20230401

ACTIVE INGREDIENTS: IOPAMIDOL 612 mg/1 mL
INACTIVE INGREDIENTS: TROMETHAMINE 1 mg/1 mL; EDETATE CALCIUM DISODIUM 0.39 mg/1 mL

ISOVUE®
Imaging Bulk Package
For use only with an automated contrast injection system, contrast management system, or contrast media transfer set approved or cleared for use with this contrast agent in this Imaging Bulk Package.
ISOVUE®-300
Iopamidol Injection 61%
ISOVUE®-370
Iopamidol Injection 76%

ISOVUE 300 and 370 are NOT FOR INTRATHECAL USE.
See Indications, and Dosage and Administration sections for further details on proper use

DIAGNOSTIC
NONIONIC RADIOPAQUE CONTRAST MEDIA

For Angiography Throughout the Cardiovascular System in Adults , Including Cerebral and Peripheral Arteriography, Coronary Arteriography and Ventriculography, Selective Visceral Arteriography and Aortography, Peripheral Venography (Phlebography), and in Pediatric Patients for Angiocardiography;
or
For Intravenous Adult and Pediatric
Computed Tomographic (CT) Imaging of the Head and Body

DESCRIPTION

ISOVUE (Iopamidol Injection) is a stable, aqueous, sterile, and nonpyrogenic solution for intravascular administration. Each bottle is to be used as an Imaging Bulk Package for dispensing multiple single doses of iopamidol injection for multiple patients, using an automated contrast injection system, contrast management system, or contrast media transfer set approved or cleared for use with this contrast agent in this Imaging Bulk Package.
Each mL of ISOVUE-300 (Iopamidol Injection 61%) provides 612 mg iopamidol with 1 mg tromethamine and 0.39 mg edetate calcium disodium. The solution contains approximately 0.043 mg (0.002 mEq) sodium and 300 mg organically bound iodine per mL.
Each mL of ISOVUE-370 (Iopamidol Injection 76%) provides 755 mg iopamidol with 1 mg tromethamine and 0.48 mg edetate calcium disodium. The solution contains approximately 0.053 mg (0.002 mEq) sodium and 370 mg organically bound iodine per mL.

The pH of ISOVUE contrast media has been adjusted to 6.5-7.5 with hydrochloric acid and/or sodium hydroxide. Pertinent physicochemical data are noted below. ISOVUE (Iopamidol Injection) is hypertonic as compared to plasma and cerebrospinal fluid (approximately 285 and 301 mOsm/kg water, respectively).

Iopamidol
Parameter | 61% | 76%
Concentration (mg iodine/mL) | 300 | 370
Osmolality @ 37° C (mOsm/kg water) | 616 | 796
Viscosity (cP) @ 37° C | 4.7 | 9.4
@ 20° C | 8.8 | 20.9
Specific Gravity @ 37° C | 1.339 | 1.405

Iopamidol is designated chemically as (S)-N,N’-bis[2-hydroxy-1-(hydroxymethyl)-ethyl]-2,4,6-triiodo-5-lactamidoisophthalamide. Structural formula:

MW 777.09
C17H22I3N3O8
CAS-60166-93-0
Organically Bound Iodine: 49%

CLINICAL PHARMACOLOGY

Intravascular injection of a radiopaque diagnostic agent opacifies those vessels in the path of flow of the contrast medium, permitting radiographic visualization of the internal structures of the human body until significant hemodilution occurs.
Following intravascular injection, radiopaque diagnostic agents are immediately diluted in the circulating plasma. Calculations of apparent volume of distribution at steady-state indicate that iopamidol is distributed between the circulating blood volume and other extracellular fluid; there appears to be no significant deposition of iopamidol in tissues. Uniform distribution of iopamidol in extracellular fluid is reflected by its demonstrated utility in computed tomographic imaging of the head and body following intravenous administration.
The pharmacokinetics of intravenously administered iopamidol in normal subjects conforms to an open two-compartment model with first order elimination (a rapid alpha phase for drug distribution and a slow beta phase for drug elimination). The elimination serum or plasma half-life is approximately two hours; the half-life is not dose dependent. No significant metabolism, deiodination, or biotransformation occurs.
Iopamidol is excreted mainly through the kidneys following intravascular administration. In patients with impaired renal function, the elimination half-life is prolonged dependent upon the degree of impairment. In the absence of renal dysfunction, the cumulative urinary excretion for iopamidol, expressed as a percentage of administered intravenous dose, is approximately 35 to 40 percent at 60 minutes, 80 to 90 percent at 8 hours, and 90 percent or more in the 72- to 96-hour period after administration. In normal subjects, approximately one percent or less of the administered dose appears in cumulative 72- to 96-hour fecal specimens.
ISOVUE may be visualized in the renal parenchyma within 30-60 seconds following rapid intravenous administration. Opacification of the calyces and pelves in patients with normal renal function becomes apparent within 1 to 3 minutes, with optimum contrast occurring between 5 and 15 minutes. In patients with renal impairment, contrast visualization may be delayed.
Iopamidol displays little tendency to bind to serum or plasma proteins.
No evidence of in vivo complement activation has been found in normal subjects.
Animal studies indicate that iopamidol does not cross the blood-brain barrier to any significant extent following intravascular administration.
ISOVUE (Iopamidol Injection) enhances computed tomographic brain imaging through augmentation of radiographic efficiency. The degree of enhancement of visualization of tissue density is directly related to the iodine content in an administered dose; peak iodine blood levels occur immediately following rapid injection of the dose. These levels fall rapidly within five to ten minutes. This can be accounted for by the dilution in the vascular and extracellular fluid compartments which causes an initial sharp fall in plasma concentration. Equilibration with the extracellular compartments is reached in about ten minutes, thereafter, the fall becomes exponential. Maximum contrast enhancement frequently occurs after peak blood iodine levels are reached. The delay in maximum contrast enhancement can range from five to forty minutes depending on the peak iodine levels achieved and the cell type of the lesion. This lag suggests that radiographic contrast enhancement is at least in part dependent on the accumulation of iodine within the lesion and outside the blood pool, although the mechanism by which this occurs is not clear. The radiographic enhancement of nontumoral lesions, such as arteriovenous malformations and aneurysms, is probably dependent on the iodine content of the circulating blood pool.
In CT head imaging, ISOVUE (Iopamidol Injection) does not accumulate in normal brain tissue due to the presence of the “blood-brain” barrier. The increase in x-ray absorption in normal brain is due to the presence of contrast agent within the blood pool. A break in the blood-brain barrier such as occurs in malignant tumors of the brain allows the accumulation of the contrast medium within the interstitial tissue of the tumor. Adjacent normal brain tissue does not contain the contrast medium.
In nonneural tissues (during computed tomography of the body), iopamidol diffuses rapidly from the vascular into the extravascular space. Increase in x-ray absorption is related to blood flow, concentration of the contrast medium, and extraction of the contrast medium by interstitial tissue of tumors since no barrier exists. Contrast enhancement is thus due to the relative differences in extravascular diffusion between normal and abnormal tissue, quite different from that in the brain.
The pharmacokinetics of iopamidol in both normal and abnormal tissue have been shown to be variable. Contrast enhancement appears to be greatest soon after administration of the contrast medium, and following intraarterial rather than intravenous administration. Thus, greatest enhancement can be detected by a series of consecutive two- to three-second scans performed just after injection (within 30 to 90 seconds), i.e., dynamic computed tomographic imaging.

INDICATIONS AND USAGE

ISOVUE (Iopamidol Injection) is indicated for angiography throughout the cardiovascular system in adults, including cerebral and peripheral arteriography, coronary arteriography and ventriculography, selective visceral arteriography and aortography, peripheral venography (phlebography), and in pediatric patients for angiocardiography; or for intravenous use in adult and pediatric for computed tomographic (CT) imaging of the head and body (see below).

CT Head Imaging
ISOVUE may be used to refine diagnostic precision in areas of the brain which may not otherwise have been satisfactorily visualized.

Tumors
ISOVUE may be useful to investigate the presence and extent of certain malignancies such as: gliomas including malignant gliomas, glioblastomas, astrocytomas, oligodendrogliomas and gangliomas, ependymomas, medulloblastomas, meningiomas, neuromas, pinealomas, pituitary adenomas, craniopharyngiomas, germinomas, and metastatic lesions. The usefulness of contrast enhancement for the investigation of the retrobulbar space and in cases of low grade or infiltrative glioma has not been demonstrated.
In calcified lesions, there is less likelihood of enhancement. Following therapy, tumors may show decreased or no enhancement.
The opacification of the inferior vermis following contrast media administration has resulted in false-positive diagnosis in a number of otherwise normal studies.

Nonneoplastic Conditions
ISOVUE may be beneficial in the image enhancement of nonneoplastic lesions. Cerebral infarctions of recent onset may be better visualized with contrast enhancement, while some infarctions are obscured if contrast media are used. The use of iodinated contrast media results in contrast enhancement in about 60 percent of cerebral infarctions studied from one to four weeks from the onset of symptoms.
Sites of active infection may also be enhanced following contrast media administration.
Arteriovenous malformations and aneurysms will show contrast enhancement. For these vascular lesions, the enhancement is probably dependent on the iodine content of the circulating blood pool.
Hematomas and intraparenchymal bleeders seldom demonstrate any contrast enhancement. However, in cases of intraparenchymal clot, for which there is no obvious clinical explanation, contrast media administration may be helpful in ruling out the possibility of associated arteriovenous malformation.

CT Body Imaging
ISOVUE (Iopamidol Injection) may be used for enhancement of computed tomographic images for detection and evaluation of lesions in the liver, pancreas, kidneys, aorta, mediastinum, abdominal cavity, pelvis and retroperitoneal space.
Enhancement of computed tomography with ISOVUE may be of benefit in establishing diagnoses of certain lesions in these sites with greater assurance than is possible with CT alone, and in supplying additional features of the lesions (e.g., hepatic abscess delineation prior to percutaneous drainage). In other cases, the contrast agent may allow visualization of lesions not seen with CT alone (e.g. tumor extension), or may help to define suspicious lesions seen with unenhanced CT (e.g., pancreatic cyst).
Contrast enhancement appears to be greatest within 60 to 90 seconds after bolus administration of contrast agent. Therefore, utilization of a continuous scanning technique (“dynamic CT scanning”) may improve enhancement and diagnostic assessment of tumor and other lesions such as an abscess, occasionally revealing unsuspected or more extensive disease. For example, a cyst may be distinguished from a vascularized solid lesion when precontrast and enhanced scans are compared; the nonperfused mass shows unchanged x-ray absorption (CT number). A vascularized lesion is characterized by an increase in CT number in the few minutes after a bolus of intravascular contrast agent; it may be malignant, benign, or normal tissue, but would probably not be a cyst, hematoma, or other nonvascular lesion.
Because unenhanced scanning may provide adequate diagnostic information in the individual patient, the decision to employ contrast enhancement, which may be associated with risk and increased radiation exposure, should be based upon a careful evaluation of clinical, other radiological, and unenhanced CT findings.

CONTRAINDICATIONS

None.

WARNINGS

Severe Adverse Events-lnadvertent Intrathecal Administration
Serious adverse reactions have been reported due to the inadvertent intrathecal administration of iodinated contrast media that are not indicated for intrathecal use.
These serious adverse reactions include: death, convulsions, cerebral hemorrhage, coma, paralysis, arachnoiditis, acute renal failure, cardiac arrest, seizures, rhabdomyolysis, hyperthermia, and brain edema. Special attention must be given to insure that this drug product is not inadvertently administered intrathecally.

General

Nonionic iodinated contrast media inhibit blood coagulation, in vitro, less than ionic contrast media. Clotting has been reported when blood remains in contact with syringes containing nonionic contrast media.
Serious, rarely fatal, thromboembolic events causing myocardial infarction and stroke have been reported during angiographic procedures with both ionic and nonionic contrast media. Therefore, meticulous intravascular administration technique is necessary, particularly during angiographic procedures, to minimize thromboembolic events. Numerous factors, including length of procedure, catheter and syringe material, underlying disease state, and concomitant medications may contribute to the development of thromboembolic events. For these reasons, meticulous angiographic techniques are recommended including close attention to guidewire and catheter manipulation, use of manifold systems and/or three way stopcocks, frequent catheter flushing with heparinized saline solutions, and minimizing the length of the procedure. The use of plastic syringes in place of glass syringes has been reported to decrease but not eliminate the likelihood of in vitro clotting.
Caution must be exercised in patients with severely impaired renal function, those with combined renal and hepatic disease, or anuria, particularly when larger doses are administered.
Radiopaque diagnostic contrast agents are potentially hazardous in patients with multiple myeloma or other paraproteinemia, particularly in those with therapeutically resistant anuria. Myeloma occurs most commonly in persons over age 40. Although neither the contrast agent nor dehydration has been proved separately to be the cause of anuria in myelomatous patients, it has been speculated that the combination of both may be causative. The risk in myelomatous patients is not a contraindication; however, special precautions are required.
Contrast media may promote sickling in individuals who are homozygous for sickle cell disease when injected intravenously or intraarterially.
Administration of radiopaque materials to patients known or suspected of having pheochromocytoma should be performed with extreme caution. If, in the opinion of the physician, the possible benefits of such procedures outweigh the considered risks, the procedures may be performed; however, the amount of radiopaque medium injected should be kept to an absolute minimum. The blood pressure should be assessed throughout the procedure and measures for treatment of a hypertensive crisis should be available. These patients should be monitored very closely during contrast enhanced procedures.
Reports of thyroid storm following the use of iodinated radiopaque diagnostic agents in patients with hyperthyroidism or with an autonomously functioning thyroid nodule suggest that this additional risk be evaluated in such patients before use of any contrast medium.

Thyroid Dysfunction in Pediatric Patients 0 to 3 Years of Age: Thyroid dysfunction characterized by hypothyroidism or transient thyroid suppression has been reported after both single exposure and multiple exposures to iodinated contrast media in pediatric patients 0 to 3 years of age.
Younger age, very low birth weight, prematurity, underlying medical conditions affecting thyroid function, admission to neonatal or pediatric intensive care units, and congenital cardiac conditions are associated with an increased risk of hypothyroidism after ICM exposure. Pediatric patients with congenital cardiac conditions may be at greatest risk given that they often require high doses of contrast during invasive cardiac procedures.
An underactive thyroid during early life may be harmful for cognitive and neurological development and may require thyroid hormone replacement therapy. After exposure to ICM, individualize thyroid function monitoring based on underlying risk factors, especially in term and preterm neonates.

Severe Cutaneous Adverse Reactions: Severe cutaneous adverse reactions (SCAR) may develop from 1 hour to several weeks after intravascular contrast agent administration. These reactions include Stevens-Johnson syndrome and toxic epidermal necrolysis (SJS/TEN), acute generalized exanthematous pustulosis (AGEP) and drug reaction with eosinophilia and systemic symptoms (DRESS). Reaction severity may increase and time to onset may decrease with repeat administration of contrast agent; prophylactic medications may not prevent or mitigate severe cutaneous adverse reactions. Avoid administering ISOVUE to patients with a history of a severe cutaneous adverse reaction to ISOVUE.

PRECAUTIONS

General

Diagnostic procedures which involve the use of any radiopaque agent should be carried out under the direction of personnel with the prerequisite training and with a thorough knowledge of the particular procedure to be performed. Appropriate facilities should be available for coping with any complication of the procedure, as well as for emergency treatment of severe reaction to the contrast agent itself. After parenteral administration of a radiopaque agent, competent personnel and emergency facilities should be available for at least 30 to 60 minutes since severe delayed reactions may occur. Caution should be exercised in hydrating patients with underlying conditions that may be worsened by fluid overload, such as congestive heart failure.
Preparatory dehydration is dangerous and may contribute to acute renal failure in patients with advanced vascular disease, diabetic patients, and in susceptible nondiabetic patients (often elderly with preexisting renal disease). Patients should be well hydrated prior to and following iopamidol administration.
The possibility of a reaction, including serious, life-threatening, fatal, anaphylactoid or cardiovascular reactions, should always be considered (see ADVERSE REACTIONS). Patients at increased risk include those with a history of a previous reaction to a contrast medium, patients with a known sensitivity to iodine per se, and patients with a known clinical hypersensitivity (bronchial asthma, hay fever, and food allergies). The occurrence of severe idiosyncratic reactions has prompted the use of several pretesting methods. However, pretesting cannot be relied upon to predict severe reactions and may itself be hazardous for the patient. It is suggested that a thorough medical history with emphasis on allergy and hypersensitivity, prior to the injection of any contrast medium, may be more accurate than pretesting in predicting potential adverse reactions. A positive history of allergies or hypersensitivity does not arbitrarily contraindicate the use of a contrast agent where a diagnostic procedure is thought essential, but caution should be exercised. Premedication with antihistamines or corticosteroids to avoid or minimize possible allergic reactions in such patients should be considered. Recent reports indicate that such pretreatment does not prevent serious life-threatening reactions but may reduce both their incidence and severity.
Pre-existing conditions, such as pacemakers or cardiac medications, specifically beta-blockers, may mask or alter the signs or symptoms of an anaphylactoid reaction, as well as masking or altering the response to particular medications used for treatment. For example, beta-blockers inhibit a tachycardiac response, and can lead to the incorrect diagnosis of a vasovagal rather than an anaphylactoid reaction. Special attention to this possibility is particularly critical in patients suffering from serious, life-threatening reactions.
General anesthesia may be indicated in the performance of some procedures in selected patients; however, a higher incidence of adverse reactions has been reported with radiopaque media in anesthetized patients, which may be attributable to the inability of the patient to identify untoward symptoms, or to the hypotensive effect of anesthesia which can reduce cardiac output and increase the duration of exposure to the contrast agent.
Even though the osmolality of iopamidol is low compared to diatrizoate or iothalamate based ionic agents of comparable iodine concentration, the potential transitory increase in the circulatory osmotic load in patients with congestive heart failure requires caution during injection. These patients should be observed for several hours following the procedure to detect delayed hemodynamic disturbances. Injection site pain and swelling may occur. In the majority of cases it is due to extravasation of contrast medium. Reactions are usually transient and recover without sequelae. However, inflammation and even skin necrosis have been seen on very rare occasions.
In angiographic procedures, the possibility of dislodging plaques or damaging or perforating the vessel wall, or inducing vasospasm, and or subsequent ischemic events, should be borne in mind during catheter manipulations and contrast medium injection. Test injections to ensure proper catheter placement are suggested.
Selective coronary arteriography should be performed only in selected patients and those in whom the expected benefits outweigh the procedural risk. The inherent risks of angiocardiography in patients with chronic pulmonary emphysema must be weighed against the necessity for performing this procedure. Angiography should be avoided whenever possible in patients with homocystinuria, because of the risk of inducing thrombosis and embolism. See also Pediatric Use.
In addition to the general precautions previously described, special care is required when venography is performed in patients with suspected thrombosis, phlebitis, severe ischemic disease, local infection or a totally obstructed venous system.
Extreme caution during injection of contrast media is necessary to avoid extravasation and fluoroscopy is recommended. This is especially important in patients with severe arterial or venous disease.

Information for Patients

Patients receiving injectable radiopaque diagnostic agents should be instructed to:

1. Inform your physician if you are pregnant.
2. Inform your physician if you are diabetic or if you have multiple myeloma, pheochromocytoma, homozygous sickle cell disease, or known thyroid disorder (see WARNINGS).
3. Inform your physician if you are allergic to any drugs, food, or if you had any reactions to previous injections of substances used for x-ray procedures (see PRECAUTIONS-General).
4. Inform your physician about any other medications you are currently taking, including nonprescription drugs, before you have this procedure.
5. Advise patients to inform their physician if they develop a rash after receiving Isovue.
6. Advise parents/caregivers about the risk of developing thyroid dysfunction after ISOVUE administration. Advise parents/caregivers about when to seek medical care for their child to monitor for thyroid function (see WARNINGS).

Drug Interactions

Renal toxicity has been reported in a few patients with liver dysfunction who were given oral cholecystographic agents followed by intravascular contrast agents. Administration of intravascular agents should therefore be postponed in any patient with a known or suspected hepatic or biliary disorder who has recently received a cholecystographic contrast agent.
Other drugs should not be admixed with iopamidol.

Drug/Laboratory Test Interactions

The results of PBI and radioactive iodine uptake studies, which depend on iodine estimations, will not accurately reflect thyroid function for up to 16 days following administration of iodinated contrast media. However, thyroid function tests not depending on iodine estimations, e.g., T3 resin uptake and total or free thyroxine (T4) assays are not affected.
Any test which might be affected by contrast media should be performed prior to administration of the contrast medium.

Laboratory Test Findings

In vitro studies with animal blood showed that many radiopaque contrast agents, including iopamidol, produced a slight depression of plasma coagulation factors including prothrombin time, partial thromboplastin time, and fibrinogen, as well as a slight tendency to cause platelet and/or red blood cell aggregation (see PRECAUTIONS-General).
Transitory changes may occur in red cell and leucocyte counts, serum calcium, serum creatinine, serum glutamic oxaloacetic transaminase (SGOT), and uric acid in urine; transient albuminuria may occur.
These findings have not been associated with clinical manifestations.

Carcinogenesis, Mutagenesis, Impairment of Fertility

Long-term studies in animals have not been performed to evaluate carcinogenic potential. No evidence of genetic toxicity was obtained in in vitro tests.

Pregnancy: Teratogenic Effects

TERATOGENIC EFFECTS

Reproduction studies have been performed in rats and rabbits at doses up to 2.7 and 1.4 times the maximum recommended human dose (1.48 gI/kg in a 50 kg individual), respectively, and have revealed no evidence of impaired fertility or harm to the fetus due to iopamidol. There are, however, no adequate and well-controlled studies in pregnant women. Because animal reproduction studies are not always predictive of human response, this drug should be used during pregnancy only if clearly needed.

Nursing Mothers

It is not known whether this drug is excreted in human milk. Because many drugs are excreted in human milk, caution should be exercised when iopamidol is administered to a nursing woman.

Pediatric Use

Safety and effectiveness in children has been established in pediatric angiocardiography and computed tomography (head and body). Pediatric patients at higher risk of experiencing adverse events during contrast medium administration may include those having asthma, a sensitivity to medication and/or allergens, cyanotic heart disease, congestive heart failure, a serum creatinine greater than 1.5 mg/dL or those less than 12 months of age.
Thyroid function tests indicative of thyroid dysfunction, characterized by hypothyroidism or transient thyroid suppression have been uncommonly reported following iodinated contrast media administration in pediatric patients, including term and preterm neonates; some patients were treated for hypothyroidism. After exposure to iodinated contrast media, individualize thyroid function monitoring in pediatric patients 0 to 3 years of age based on underlying risk factors, especially in term and preterm neonates (see WARNINGS and ADVERSE REACTIONS).

ADVERSE REACTIONS

Adverse reactions following the use of iopamidol are usually mild to moderate, self-limited, and transient.
In angiocardiography (597 patients), the adverse reactions with an estimated incidence of one percent or higher are: hot flashes 3.4%; angina pectoris 3.0%; flushing 1.8%; bradycardia 1.3%; hypotension 1.0%; hives 1.0%.
In a clinical trial with 76 pediatric patients undergoing angiocardiography, 2 adverse reactions (2.6%) both remotely attributed to the contrast media were reported. Both patients were less than 2 years of age, both had cyanotic heart disease with underlying right ventricular abnormalities and abnormal pulmonary circulation. In one patient pre-existing cyanosis was transiently intensified following contrast media administration. In the second patient pre-existing decreased peripheral perfusion was intensified for 24 hours following the examination. (See “PRECAUTIONS” Section for information on high risk nature of these patients.)
Intravascular injection of contrast media is frequently associated with the sensation of warmth and pain especially in peripheral arteriography and venography; pain and warmth are less frequent and less severe with ISOVUE (Iopamidol Injection) than with diatrizoate meglumine and diatrizoate sodium injection.
The following table of incidence of reactions is based on clinical studies with ISOVUE in about 2246 patients.

Adverse Reactions
 | Estimated Overall Incidence
System | > 1% | ≤ 1%
Cardiovascular | none | tachycardia hypotension hypertension myocardial ischemia circulatory collapse S-T segment depression bigeminy extrasystoles ventricular fibrillation angina pectoris bradycardia transient ischemic attack thrombophlebitis
Nervous | pain (2.8%) burning sensation (1.4%) | vasovagal reaction tingling in arms grimace faintness
Digestive | nausea (1.2%) | vomiting anorexia
Respiratory | none | throat constriction dyspnea pulmonary edema
Skin and Appendages | none | rash urticaria pruritus flushing
Body as a Whole | hot flashes (1.5%) | headache fever chills excessive sweating back spasm
Special Senses | warmth (1.1%) | taste alterations nasal congestion visual disturbances
Urogenital | none | urinary retention

Regardless of the contrast agent employed, the overall estimated incidence of serious adverse reactions is higher with coronary arteriography than with other procedures. Cardiac decompensation, serious arrhythmias, or myocardial ischemia or infarction have been reported with ISOVUE and may occur during coronary arteriographyand left ventriculography.
Following coronary and ventricular injections, certain electrocardiographic changes (increased QTc, increased R-R, T-wave amplitude) and certain hemodynamic changes (decreased systolic pressure) occurred less frequently with ISOVUE (Iopamidol Injection) than with diatrizoate meglumine and diatrizoate sodium injection; increased LVEDP occurred less frequently after ventricular iopamidol injections.
In aortography, the risks of procedures also include injury to the aorta and neighboring organs, pleural puncture, renal damage including infarction and acute tabular necrosis with oliguria and anuria, accidental selective filling of the right renal artery during the translumbar procedure in the presence of pre-existing renal disease, retroperitoneal hemorrhage from the translumbar approach, and spinal cord injury and pathology associated with the syndrome of transverse myelitis.
The following adverse reactions have been reported for Iopamidol: Cardiovascular: arrhythmia, arterial spasms, flushing, vasodilation, chest pain, cardiopulmonary arrest; Nervous System: confusion, paresthesia, dizziness, temporary cortical blindness, temporary amnesia, convulsions, paralysis, coma; Respiratory: increased cough, sneezing, asthma, apnea, laryngeal edema, chest tightness, rhinitis; Skin and Appendages: injection site pain usually due to extravasation and/or erythematous swelling, pallor, periorbital edema, facial edema; Urogenital: pain, hematuria; Special Senses: watery itchy eyes, lacrimation, conjunctivitis; Musculoskeletal: muscle spasm, involuntary leg movement; Body as a whole: tremors, malaise, anaphylactoid reaction (characterized by cardiovascular, respiratory and cutaneous symptoms), pain; Digestive: severe retching and choking, abdominal cramps. Some of these may occur as a consequence of the procedure. Other reactions may also occur with the use of any contrast agent as a consequence of the procedural hazard; these include hemorrhage or pseudoaneurysms at the puncture site, brachial plexus palsy following axillary artery injections, chest pain, myocardial infarction, and transient changes in hepatorenal chemistry tests. Arterial thrombosis, displacement of arterial plaques, venous thrombosis, dissection of the coronary vessels and transient sinus arrest are rare complications.

General Adverse Reactions To Contrast Media

Reactions known to occur with parenteral administration of iodinated ionic contrast agents (see the listing below) are possible with any nonionic agent. Approximately 95 percent of adverse reactions accompanying the use of other water-soluble intravascularly administered contrast agents are mild to moderate in degree. However, life-threatening reactions and fatalities, mostly of cardiovascular origin, have occurred. Reported incidences of death from the administration of other iodinated contrast media range from 6.6 per 1 million (0.00066 percent) to 1 in 10,000 patients (0.01 percent). Most deaths occur during injection or 5 to 10 minutes later, the main feature being cardiac arrest with cardiovascular disease as the main aggravating factor. Isolated reports of hypotensive collapse and shock are found in the literature. The incidence of shock is estimated to be 1 out of 20,000 (0.005 percent) patients.
Adverse reactions to injectable contrast media fall into two categories: chemotoxic reactions and idiosyncratic reactions. Chemotoxic reactions result from the physicochemical properties of the contrast medium, the dose, and the speed of injection. All hemodynamic disturbances and injuries to organs or vessels perfused by the contrast medium are included in this category. Idiosyncratic reactions include all other reactions. They occur more frequently in patients 20 to 40 years old. Idiosyncratic reactions may or may not be dependent on the amount of drug injected, the speed of injection, the mode of injection, and the radiographic procedure. Idiosyncratic reactions are subdivided into minor, intermediate, and severe. The minor reactions are self-limited and of short duration; the severe reactions are life-threatening and treatment is urgent and mandatory.
The reported incidence of adverse reactions to contrast media in patients with a history of allergy is twice that for the general population. Patients with a history of previous reactions to a contrast medium are three times more susceptible than other patients. However, sensitivity to contrast media does not appear to increase with repeated examinations. Most adverse reactions to intravascular contrast agents appear within one to three minutes after the start of injection, but delayed reactions may occur. Delayed reactions, usually involving the skin, may uncommonly occur within 2-3 days (range 1-7 days) after the administration of contrast (see PRECAUTIONS-General). Delayed allergic reactions are more frequent in patients treated with immunostimulants, such as interleukin-2.
In addition to the adverse drug reactions reported for iopamidol, the following additional adverse reactions have been reported with the use of other intravascular contrast agents and are possible with the use of any water-soluble iodinated contrast agent:
Cardiovascular: cerebral hematomas, petechiae; Hematologic: neutropenia; Urogenital: osmotic nephrosis of proximal tubular cells, renal failure; Special Senses: conjunctival chemosis with infection. Endocrine: hyperthyroidism, hypothyroidism; Skin and Subcutaneous Tissue Disorders: Skin necrosis; Reactions range from mild (e.g. rash, erythema, pruritus, uticaria and skin discoloration) to severe: [e.g. Stevens-Johnson syndrome and toxic epidermal necrolysis (SJS/TEN), cute generalized exanthematous pustulosis (AGEP) and drug reaction with eosinophilia and systemic symptoms (DRESS)].

OVERDOSAGE

Treatment of an overdose of an injectable radiopaque contrast medium is directed toward the support of all vital functions, and prompt institution of symptomatic therapy.

DOSAGE AND ADMINISTRATION

General

Parenteral drug products should be inspected visually for particulate matter and discoloration prior to administration, whenever solution and container permit. Iopamidol solutions should be used only if clear and within the normal colorless to pale yellow range. Discard any product which shows signs of crystallization or damage to the container-closure system, which includes the glass container, stopper and/or crimp.

It is desirable that solutions of radiopaque diagnostic agents for intravascular use be at body temperature when injected. Sterile techniques must be used with any intravascular injection.
The transferring of ISOVUE from the ISOVUE Imaging Bulk Package container should be performed utilizing aseptic technique. The Imaging Bulk Package closure may be penetrated only one time, with a suitable sterile component of the automated contrast injection system, contrast management system, or contrast media transfer set approved or cleared for use with this Imaging Bulk Package.
Patients should be well hydrated prior to and following ISOVUE (Iopamidol Injection) administration.
As with all radiopaque contrast agents, only the lowest dose of ISOVUE necessary to obtain adequate visualization should be used. A lower dose reduces the possibility of an adverse reaction. Most procedures do not require use of either a maximum dose or the highest available concentration of ISOVUE; the combination of dose and ISOVUE concentration to be used should be carefully individualized, and factors such as age, body size, size of the vessel and its blood flow rate, anticipated pathology and degree and extent of opacification required, structure(s) or area to be examined, disease processes affecting the patient, and equipment and technique to be employed should be considered.

Cerebral Arteriography

ISOVUE-300 (Iopamidol Injection, 300 mg iodine/mL) should be used. The usual individual injection by carotid puncture or transfemoral catheterization is 8 to 12 mL, with total multiple doses up to 90 mL.

Peripheral Arteriography

ISOVUE-300 usually provides adequate visualization. For injection into the femoral artery or subclavian artery, 5 to 40 mL may be used; for injection into the aorta for a distal runoff, 25 to 50 mL may be used. Doses up to a total of 250 mL of ISOVUE-300 have been administered during peripheral arteriography.

Peripheral Venography (Phlebography)

ISOVUE-300 should be used. The usual dose is 15 mL to 100 mL per lower extremity. The combined total dose for multiple injections should not exceed 230 mL.

Selective Visceral Arteriography and Aortography

ISOVUE-370 (Iopamidol Injection, 370 mg iodine/mL) should be used. Doses up to 50 mL may be required for injection into the larger vessels such as the aorta or celiac artery; doses up to 10 mL may be required for injection into the renal arteries. Often lower doses will be sufficient. The combined total dose for multiple injections has not exceeded 225 mL.

Pediatric Angiocardiography

ISOVUE-370 should be used. Pediatric angiocardiography may be performed by injection into a large peripheral vein or be direct characterization of the heart. The usual dose range for single injections is provided in the following table:

Single Injection
Usual Dose Range
Age | mL
<2 years | 10–15
2–9 years | 15–30
10–18 years | 20–50

The usual recommended dose for cumulative injections is provided in the following table.

Cumulative Injection
Usual Recommended Dose
Age | mL
<2 years | 40
2–4 years | 50
5–9 years | 100
10–18 years | 125

Coronary Arteriography and Ventriculography

ISOVUE-370 should be used. The usual dose for selective coronary artery injections is 2 to 10 mL. The usual dose for ventriculography, or for nonselective opacification of multiple coronary arteries following injection at the aortic root is 25 to 50 mL. The total dose for combined procedures has not exceeded 200 mL. EKG monitoring is essential.

Computed Tomography

CT OF THE HEAD: The suggested dose for ISOVUE-300 is 100 to 200 mL by intravenous administration. Imaging may be performed immediately after completion of administration.
CT OF THE BODY: The usual adult dose range for ISOVUE-300 is 100-to 200 mL administered by rapid intravenous infusion or bolus injection.
Equivalent doses of ISOVUE-370 based on organically bound iodine content may also be used.
The total dose for either CT procedure should not exceed 60 grams of iodine.

Pediatric Computed Tomography

The dosage recommended for use in children for contrast enhanced computed tomography is 1.0 mL/kg to 3.0 mL/kg for ISOVUE-300. It should not be necessary to exceed a total dose of 30 grams of iodine.

Drug Incompatibilities

Many radiopaque contrast agents are incompatible in vitro with some antihistamines and many other drugs; therefore, no other pharmaceuticals should be admixed with contrast agents.

DRUG HANDLING

Parenteral drug products should be inspected visually for particulate matter and discoloration prior to administration, whenever solution and container permit. Iopamidol solutions should be used only if clear and within the normal colorless to pale yellow range. Discard any product which shows signs of crystallization or damage to the container-closure system, which includes the glass container, stopper and/or crimp.

Directions for Proper Use of the ISOVUE Imaging Bulk Package

The ISOVUE Imaging Bulk Package is used for dispensing multiple single doses of iopamidol injection for multiple patients, using an automated contrast injection system contrast management system, or contrast media transfer set approved or cleared for use with this contrast agent in this Imaging Bulk Package. Preparations of 0.9% Sodium Chloride Injection USP, with a sterile port for an intravenous administration set, are to be used with the ISOVUE Imaging Bulk Package and automated contrast injection systems or contrast management systems approved for use with the ISOVUE Imaging Bulk Package. Please see drug and device labeling for information on devices indicated for use with this Imaging Bulk Package and techniques to help assure safe use.

1. The ISOVUE Imaging Bulk Package is to be used only in a room designated for radiological procedures that involve intravascular administration of a contrast agent.
2. The transferring of ISOVUE from the Imaging Bulk Package should be performed utilizing aseptic technique. Prior to penetrating the container closure, swab the face of the container stopper with 70% isopropyl alcohol. The container closure may be penetrated only one time with a suitable sterile component of the automated contrast injection system, contrast management system, or contrast media transfer set approved or cleared for use with this Imaging Bulk Package.
3. Once the Imaging Bulk Package is punctured, it should not be removed from the work area during the entire period of use, and the bottle should be maintained in an inverted position such that container contents are in continuous contact with the dispensing set.
4. A maximum use time of 10 hours from initial closure entry is permitted to complete fluid transfer. Any unused ISOVUE injection must be discarded 10 hours after initial puncture of the Imaging Bulk Package.
5. After the container closure is punctured, if the integrity of the Imaging Bulk Package and the delivery system cannot be assured though direct continuous supervision, the Imaging Bulk Package and all associated disposables for the automated contrast injection system, contrast management system, or contrast media transfer set should be discarded.
6. Storage temperature of the ISOVUE Imaging Bulk Package container after the closure has been entered should not exceed 25° C (77° F); however, it is desirable that the contents be warmed to body temperature prior to injection.
7. If 0.9% Sodium Chloride Injection USP is used, prepare the intravenous port in accordance with the DOSAGE AND ADMINISTRATION section of the approved prescribing information of the product.
8. Multiple-dose use of 0.9% Sodium Chloride Injection USP:
  - 0.9% Sodium Chloride Injection USP should only be used to deliver multiple doses to multiple patients when used with an automated contrast injection system or contrast management system approved or cleared for multiple-dose use of 0.9% Sodium Chloride Injection.
  - The intravenous administration port of the sodium chloride container may be penetrated only one time with a suitable sterile component of the contrast management system approved for use with the ISOVUE Imaging Bulk Package, using aseptic technique. A maximum use time of 10 hours from initial closure entry is permitted to complete the fluid transfer. Any unused sodium chloride must be discarded 10 hours after initial puncture of the 0.9% Sodium Chloride Injection USP container. The container of 0.9% Sodium Chloride Injection USP is to be used only in an area designated for radiological procedures that involve intravascular administration of contrast. All above instructions in c. through e. for the ISOVUE Imaging Bulk Package should be followed for the 0.9% Sodium Chloride Injection USP container. Strap the saline tag provided with the ISOVUE Imaging Bulk Package on the 0.9% Sodium Chloride Injection USP container.
9. Single-dose use of 0.9% Sodium Chloride Injection USP: Use in accordance with the manufacturers Prescribing Information.

HOW SUPPLIED

ISOVUE-300 (Iopamidol Injection 61%)
Ten 200 mL Imaging Bulk Packages (NDC 0270-1315-45)
Six 500 mL Imaging Bulk Packages (NDC 0270-1315-95)
ISOVUE-370 (Iopamidol Injection 76%)
Ten 200 mL Imaging Bulk Packages (NDC 0270-1316-45)
Six 500 mL Imaging Bulk Packages (NDC 0270-1316-95)

Storage

Store at 20-25° C (68-77° F). [See USP]. Protect from light.

ISOVUE is a registered trademark of Bracco Diagnostics Inc.

Rx Only

Manufactured for
Bracco Diagnostics Inc. – Monroe Township, NJ 08831
by BIPSO GmbH
78224 Singen (Germany)

Revised April 2023

CL72D08

PACKAGE LABEL

Isovue-300 200 mL Imaging Bulk Pack

Isovue-300 1 box • 10 Imaging Bulk Packages-200 mL each

PACKAGE LABEL

Isovue-370 200 mL Imaging Bulk Pack

Isovue–370 1 box • 10 Imaging Bulk Packages-200 mL each

Isovue-370 500 mL Imaging Bulk Pack

Isovue–370 1 box • 6 Imaging Bulk Packages-500 mL each